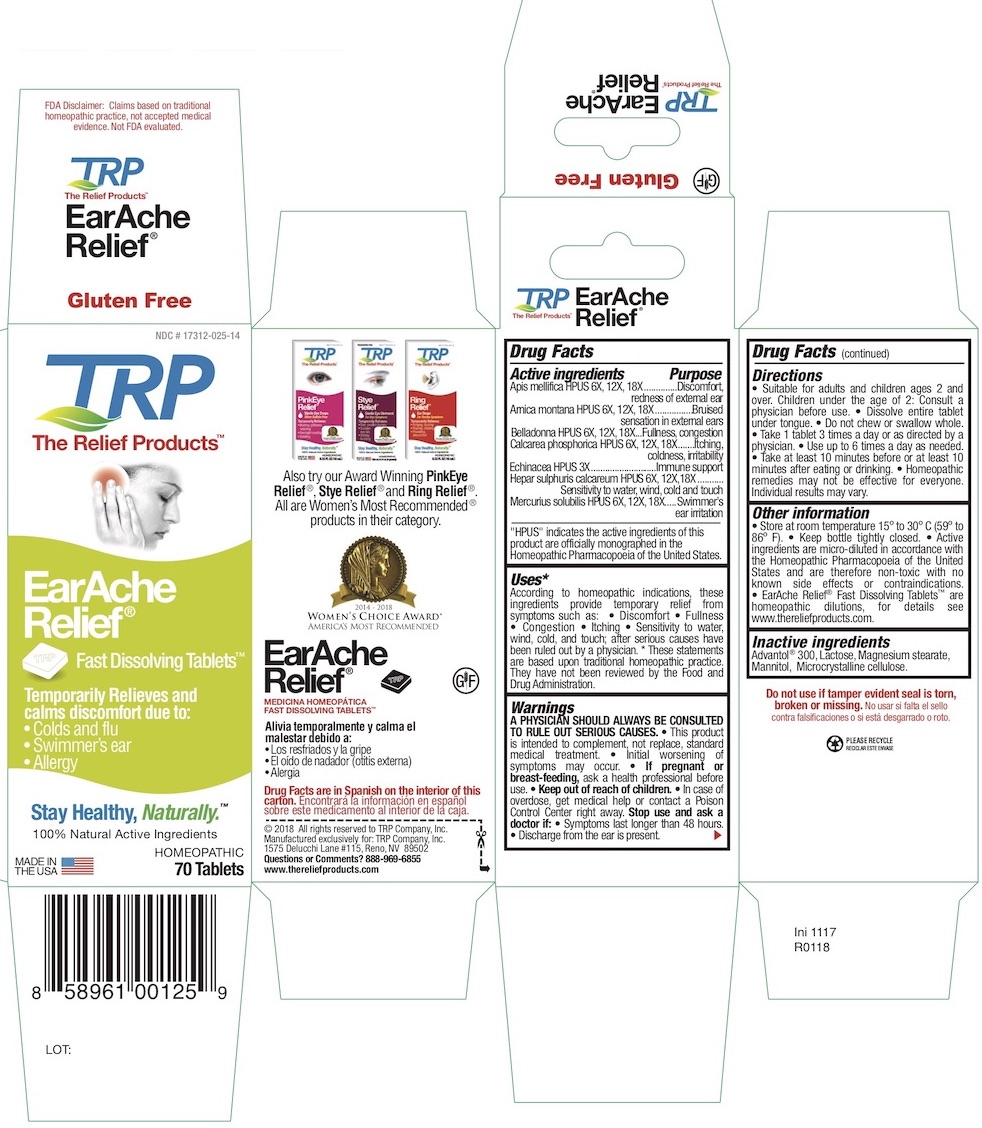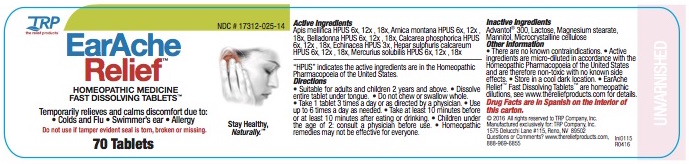 DRUG LABEL: EarAche Relief
NDC: 17312-025 | Form: TABLET, ORALLY DISINTEGRATING
Manufacturer: TRP Company
Category: homeopathic | Type: HUMAN OTC DRUG LABEL
Date: 20251215

ACTIVE INGREDIENTS: APIS MELLIFERA 6 [hp_X]/1 1; ARNICA MONTANA 6 [hp_X]/1 1; ATROPA BELLADONNA 6 [hp_X]/1 1; TRIBASIC CALCIUM PHOSPHATE 6 [hp_X]/1 1; ECHINACEA, UNSPECIFIED 3 [hp_X]/1 1; CALCIUM SULFIDE 6 [hp_X]/1 1; MERCURIUS SOLUBILIS 6 [hp_X]/1 1
INACTIVE INGREDIENTS: MANNITOL; SORBITOL; CROSPOVIDONE; CELLULOSE, MICROCRYSTALLINE; COPOVIDONE; SILICON DIOXIDE; LACTOSE; MAGNESIUM STEARATE

EarAche Relief Homeopathic Fast Dissolving Tablets

ACTIVE INGREDIENT

Apis mellifica HPUS - 6x, 12x, 18x

Arnica montana HPUS - 6x, 12x, 18x

Belladonna HPUS - 6x, 12x, 18x

Calcarea phosphorica HPUS - 6x, 12x, 18x

Echinacea HPUS - 3x

Hepar sulphuris calcareum HPUS - 6x, 12x, 18x

Mercurius solubilis HPUS - 6x, 12x, 18x

HPUS indicates the active ingredients are in the Homeopathic Pharmacopoeia of the United States.

PURPOSE

Apis mellifica HPUS - Discomfort, Redness of external ear

Arnica montana - Bruised sensation in external ears

Belladonna HPUS - Fullness, Congestion

Calcarea phosphorica HPUS - Itching, Coldness, Irritability

Echinacea HPUS - Immune support

Hepar sulphuris calcareum HPUS - Sensitivity to water, wind, cold and touch

Mercurius solubilis - Swimmer’s ear irritation

Warnings

USE ONLY AFTER DIAGNOSIS BY A PHYSICIAN AND UNDER THE SUPERVISION OF A PHYSICIAN.

This product is intended to complement, not replace, standard medical treatment.

- Initial worsening of symptoms may occur.
- A physician should always be consulted to rule out serious causes.
- In case of overdose, get medical help or contact a Poison Control Center right away.

PREGNANCY OR BREAST FEEDING

If pregnant or breast-feeding, ask a health professional before use.

Directions

- Suitable for adults and children 12 years and above.
- Dissolve entire tablet under tongue.
- Do not chew or swallow whole.
- Take 1 tablet 3 times a day or as directed by a physician.
- Use up to 6 times a day as needed.
- Take at least 10 minutes before or at least 10 minutes after eating or drinking.
- Children under the age of 12: consult a physician before use.
- Homeopathic remedies may not be effective for everyone.

Other information

- There are no known contraindications.
- Active ingredients are micro-diluted in accordance with the Homeopathic Pharmacopoeia of the United States and are therefore non-toxic with no known side effects.
- Store in a cool dark location.
- EarAche Relief Fast Dissolving Tablets are homeopathic dilutions: see www.thereliefproducts.com for details.

Inactive Ingredients

Advantol® 300, Lactose, Magnesium Stearate, Mannitol, Microcrystalline Cellulose.

Questions or comments? www.thereliefproducts.com, 888-969-6855